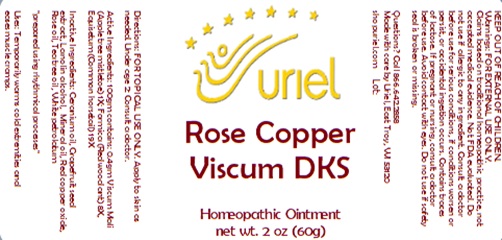 DRUG LABEL: Rose Copper Viscum DKS
NDC: 48951-8391 | Form: OINTMENT
Manufacturer: Uriel Pharmacy Inc.
Category: homeopathic | Type: HUMAN OTC DRUG LABEL
Date: 20231228

ACTIVE INGREDIENTS: EQUISETUM ARVENSE TOP 19 [hp_X]/1 g; VISCUM ALBUM FRUITING TOP 1 [hp_X]/1 g; FORMICA RUFA 8 [hp_X]/1 g
INACTIVE INGREDIENTS: CUPROUS OXIDE; ROSE OIL; PETROLATUM; GERANIUM OIL, ALGERIAN TYPE; TEA TREE OIL; CITRUS PARADISI SEED; LANOLIN; MINERAL OIL

Rose Copper Viscum DKS

INDICATIONS AND USAGE

Directions: FOR TOPICAL USE ONLY.

DOSAGE AND ADMINISTRATION

Apply to skin as needed. Under age 2: Consult a doctor.

ACTIVE INGREDIENT

Active Ingredients: 100gm contains: 0.4gm Viscum Mali (Apple tree mistletoe) 1X; Formica (Red wood ant) 8X, Equisetum (Common horsetail) 19X

INACTIVE INGREDIENT

Inactive Ingredients: Geranium oil, Grapefruit seed extract, Lanolin alcohol, Mineral oil, Red copper oxide, Rose oil, Tea tree oil, White petrolatum

"prepared using rhythmical processes"

PURPOSE

Uses: Temporarily warms cold extremities and eases muscle cramps.

KEEP OUT OF REACH OF CHILDREN.

Warnings: FOR EXTERNAL USE ONLY.
Claims based on traditional homeopathic practice, not accepted medical evidence. Not FDA evaluated. Do not use if allergic to
any ingredient. Consult a doctor before use for serious conditions, if conditions worsen or persist, or accidental ingestion occurs.
If pregnant or nursing, consult a doctor before use. Avoid contact with eyes. Do not use if safety seal is broken or missing.

Questions? Call 866.642.2858
Made with care by Uriel, East Troy, WI 53120
shopuriel.com Lot: